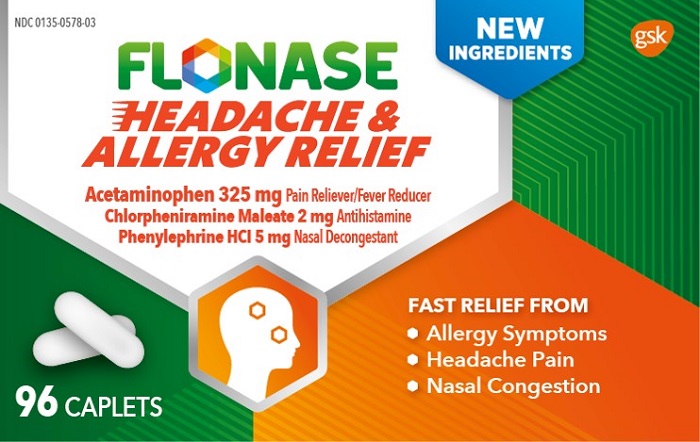 DRUG LABEL: FLONASE

NDC: 0135-0578 | Form: TABLET
Manufacturer: Haleon US Holdings LLC
Category: otc | Type: HUMAN OTC DRUG LABEL
Date: 20240408

ACTIVE INGREDIENTS: ACETAMINOPHEN 325 mg/1 1; CHLORPHENIRAMINE MALEATE 2 mg/1 1; PHENYLEPHRINE HYDROCHLORIDE 5 mg/1 1
INACTIVE INGREDIENTS: BENZYL ALCOHOL; CROSPOVIDONE, UNSPECIFIED; MAGNESIUM STEARATE; MICROCRYSTALLINE CELLULOSE; MODIFIED CORN STARCH (1-OCTENYL SUCCINIC ANHYDRIDE); POLYETHYLENE GLYCOL, UNSPECIFIED; POLYVINYL ALCOHOL, UNSPECIFIED; POVIDONE, UNSPECIFIED; STARCH, CORN; PROPYLENE GLYCOL; WATER; SILICON DIOXIDE; SODIUM STARCH GLYCOLATE TYPE A POTATO; STEARIC ACID; SUCRALOSE; TALC; TITANIUM DIOXIDE

Drug Facts

Active ingredient (in each caplet)

Acetaminophen 325 mg

Chlorpheniramine maleate 2 mg

Phenylephrine HCl 5 mg

Purposes

Pain reliever/Fever reducer

Antihistamine

Nasal decongestant

Uses

- temporarily relieves these symptoms of hay fever or other upper respiratory allergies:
- sinus congestion and pressure
- runny nose and sneezing
- minor aches and pains
- nasal congestion
- headache
- temporarily relieves these additional symptoms of hay fever:
- itching of the nose or throat
- itchy, watery eyes
- helps clear nasal passages
- helps decongest sinus openings and passages

Warnings

Liver warning:This product contains acetaminophen. Severe liver damage

may occur if you take

- more than 4,000 mg of acetaminophen in 24 hours
  - with other drugs containing acetaminophen
  - 3 or more alcoholic drinks every day while using this product

Allergy alert:Acetaminophen may cause severe skin reactions. Symptoms

may include:

- blisters
- rash
- skin reddening

If a skin reaction occurs, stop use and seek medical help right away.

Do not use

- with any other drug containing acetaminophen (prescription or nonprescription). If you are not sure whether a drug contains acetaminophen, ask a doctor or pharmacist.
- if you are now taking a prescription monoamine oxidase inhibitor (MAOI) (certain drugs for depression, psychiatric or emotional conditions, or Parkinson’s disease), or for 2 weeks after stopping the MAOI drug. If you do not know if your prescription drug contains an MAOI, ask a doctor or pharmacist before taking this product.
- if you have ever had an allergic reaction to this product or any of its ingredients

Ask a doctor before use if you have

- difficulty in urination due to enlargement of the prostate gland
- high blood pressure
- a breathing problem such as emphysema or chronic bronchitis
- heart disease
- liver disease
- thyroid disease
- glaucoma
- diabetes

Ask a doctor or pharmacist before use if you are

- taking the blood thinning drug warfarin
- taking sedatives or tranquilizers

When using this product

- do not exceed recommended dosage
- excitability may occur, especially in children
- alcohol, sedatives, and tranquilizers may increase drowsiness
- avoid alcoholic beverages
- use caution when driving a motor vehicle or operating machinery
- drowsiness may occur

Stop use and ask a doctor if

- nervousness, dizziness, or sleeplessness occur
- pain or nasal congestion gets worse or lasts more than 7 days
- new symptoms occur
- fever gets worse or lasts more than 3 days
- redness or swelling is present
- These could be signs of a serious condition.

If pregnant or breast-feeding,

ask a health professional before use.

Keep out of reach of children.

In case of overdose, get medical help or contact a Poison Control Center right away. Prompt medical attention is critical for adults as well as for children even if you do not notice any signs or symptoms.

Directions

- do not use more than directed
- adults and children 12 years of age and over:
  - take 2 caplets every 4-6 hours
  - swallow whole – do not crush, chew, or dissolve
  - do not take more than 10 caplets in 24 hours
- children under 12 years of age: ask a doctor

Other information

- store at controlled room temperature 20-25°C (68-77°F)

Inactive ingredients

benzyl alcohol, crospovidone, magnesium stearate, microcrystalline cellulose, modified corn starch, natural flavor, polyethylene glycol, polyvinyl alcohol, povidone, pregelatinized starch, propylene glycol, purified water, silicon dioxide, sodium starch glycolate, stearic acid, sucralose, talc, titanium dioxide

Questions or comments?

1-855-328-5259

Additional Information

KEEP CARTON FOR COMPLETE INFORMATION

Do not use if blister is broken or damaged.

Distributed by:

GSK Consumer Healthcare

Warren, NJ 07059

Trademarks are owned by or licensed to the GSK group of companies.

©2022 GSK group of companies or its licensor.

Principal Display Panel

NDC 0135-0578-03

FLONASE

HEADACHE &

ALLERGY RELIEF

NEW INGREDIENTS

Acetaminophen 325 mgPain Reliever/Fever Reducer

Chlorpheniramine Maleate 2 mgAntihistamine

Phenylephrine HCI 5 mgNasal Decongestant

FAST RELIEF FROM

- Allergy Symptoms
- Headache Pain
- Nasal Congestion

96CAPLETS

B-0630-778-46 ORG – Front Carton